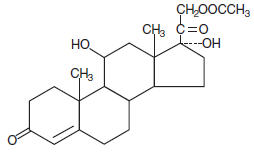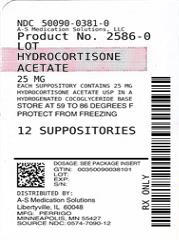 DRUG LABEL: Hydrocortisone Acetate
NDC: 50090-0381 | Form: SUPPOSITORY
Manufacturer: A-S Medication Solutions
Category: prescription | Type: HUMAN PRESCRIPTION DRUG LABEL
Date: 20190124

ACTIVE INGREDIENTS: HYDROCORTISONE ACETATE 25 mg/1 1

Hydrocortisone Acetate
Suppositories 25 mg

DESCRIPTION

Each suppository for rectal administration contains 25 mg hydrocortisone acetate USP in a hydrogenated cocoglyceride base. Hydrocortisone acetate is a corticosteroid.

Chemically, hydrocortisone acetate is pregn-4-ene-3, 20 dione, 21- (acetyloxy)-11, 17-dihydroxy-, (11β)- with the following structural formula:

CLINICAL PHARMACOLOGY

In normal subjects, about 26 percent of hydrocortisone acetate is absorbed when the hydrocortisone acetate suppository is applied to the rectum. Absorption of hydrocortisone acetate may vary across abraded or inflamed surfaces.

Topical steroids are primarily effective because of their anti-inflammatory, antipruritic and vasoconstrictive action.

INDICATIONS AND USAGE

For use in inflamed hemorrhoids, post irradiation (factitial) proctitis, as an adjunct in the treatment of chronic ulcerative colitis, cryptitis, other inflammatory conditions of the anorectum, and pruritus ani.

CONTRAINDICATIONS

Hydrocortisone acetate suppositories are contraindicated in those patients with a history of hypersensitivity to any of the components.

PRECAUTIONS

Do not use unless adequate proctologic examination is made.

If irritation develops, the product should be discontinued and appropriate therapy instituted.

In the presence of an infection, the use of an appropriate antifungal or antibacterial agent should be instituted. If a favorable response does not occur promptly, the corticosteroid should be discontinued until the infection has been adequately controlled.

No long-term studies in animals have been performed to evaluate the carcinogenic potential of corticosteroid suppositories.

PREGNANCY CATEGORY C

In laboratory animals, topical steroids have been associated with an increase in the incidence of fetal abnormalities when gestating females have been exposed to rather low dosage levels. There are no adequate and well-controlled studies in pregnant women.

It is not known whether this drug is excreted in human milk.

Until adequate studies in pregnant or lactating women have been conducted, this drug should be used during pregnancy or by nursing mothers only when clearly needed and when the potential benefits outweigh the potential risks.

ADVERSE REACTIONS

The following local adverse reactions have been reported with corticosteroid suppositories:

- Burning
- Itching
- Irritation
- Dryness

- Folliculitis
- Hypopigmentation
- Allergic Contact Dermatitis
- Secondary Infection

Drug abuse and dependence have not been reported in patients treated with hydrocortisone acetate suppositories.

OVERDOSAGE

If signs and symptoms of systemic overdosage occur, discontinue use.

DOSAGE AND ADMINISTRATION

Usual dosage:

One suppository in the rectum morning and night for two weeks, in nonspecific proctitis. In more severe cases, one suppository three times daily; or two suppositories twice daily. In factitial proctitis, recommended therapy is six to eight weeks or less, according to response.

HOW SUPPLIED

Product: 50090-0381

NDC: 50090-0381-0 1 SUPPOSITORY in a PACKET / 12 in a BOX

Manufactured By
Perrigo®
Minneapolis, MN 55427
(01-12)